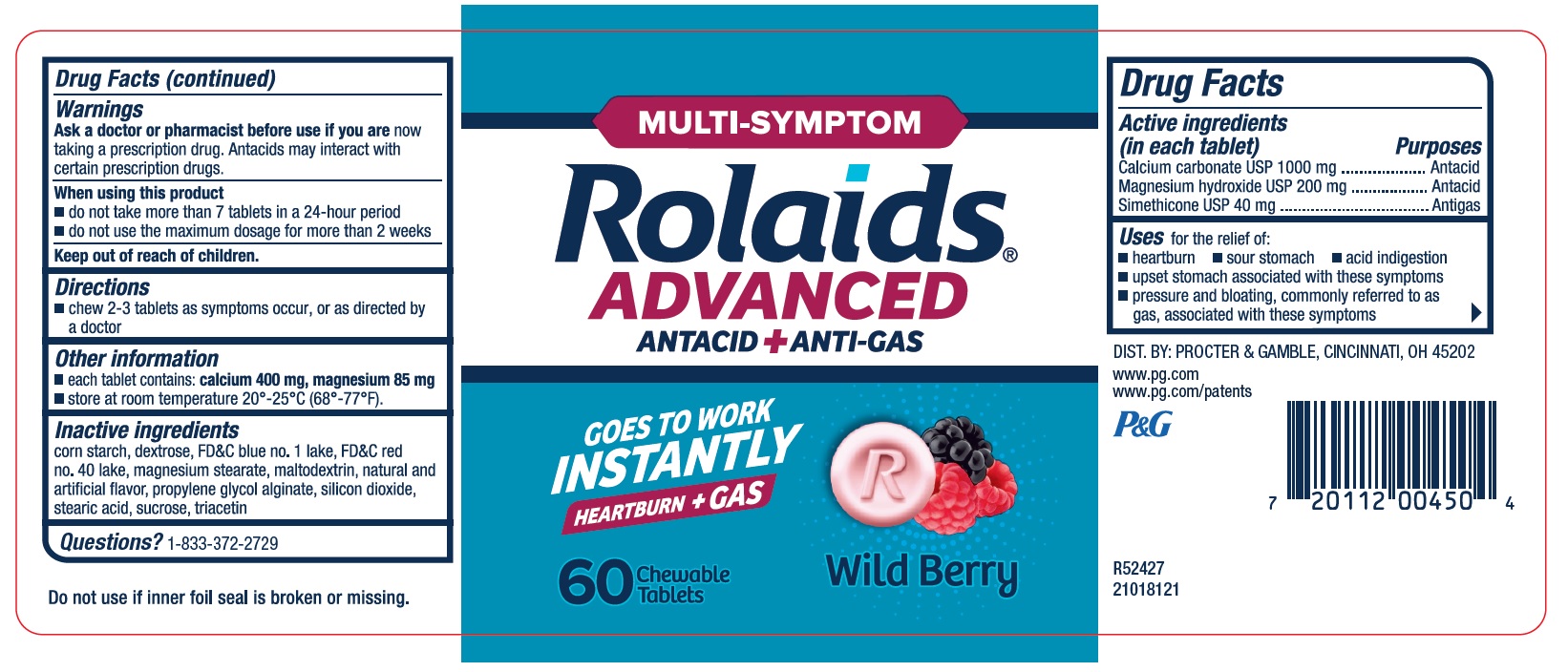 DRUG LABEL: Rolaids Multi-Symptom Advanced Antacid plus Anti-gas
NDC: 69423-826 | Form: TABLET, CHEWABLE
Manufacturer: THE PROCTER & GAMBLE MANUFACTURING COMPANY
Category: otc | Type: HUMAN OTC DRUG LABEL
Date: 20251003

ACTIVE INGREDIENTS: CALCIUM CARBONATE 1000 mg/1 1; MAGNESIUM HYDROXIDE 200 mg/1 1; DIMETHICONE 40 mg/1 1
INACTIVE INGREDIENTS: STARCH, CORN; DEXTROSE; FD&C BLUE NO. 1; FD&C RED NO. 40; MAGNESIUM STEARATE; MALTODEXTRIN; PROPYLENE GLYCOL ALGINATE; SILICON DIOXIDE; STEARIC ACID; SUCROSE; TRIACETIN; ALUMINUM OXIDE

Rolaids® Multi-Symptom Advanced Antacid + Anti-Gas, Wild Berry

Multi-Symptom

Rolaids Advanced

Antacid + Anti-Gas Chewable Tablets

(Wild Berry)

Drug Facts

Active ingredients (in each tablet)

Calcium carbonate USP 1000 mg

Magnesium hydroxide USP 200 mg

Simethicone USP 40 mg

Purposes

Antacid

Antacid

Antigas

Uses

for the relief of: ■ heartburn ■ sour stomach ■ acid indigestion

■ upset stomach associated with these symptoms

■ pressure and bloating, commonly referred to as gas, associated with these symptoms

Warnings

Ask a doctor or pharmacist before use if you are

now taking a prescription drug. Antacids may interact with certain prescription drugs.

When using this product

■ do not take more than 7 tablets in a 24-hour period

■ do not use the maximum dosage for more than 2 weeks

Directions

■ chew 2-3 tablets as symptoms occur, or as directed by a doctor

Other information

■ each tablet contains: calcium 400 mg, magnesium 85 mg

■ store at room temperature 20°-25°C (68°-77°F).

Inactiveingredients

corn starch, dextrose, FD&C blue no. 1 lake, FD&C red no. 40 lake, magnesium stearate, maltodextrin, natural and artificial flavor, propylene glycol alginate, silicon dioxide, stearic acid, sucrose, triacetin

Questions?

1-833-372-2729

Tamper Evident

Do not use if inner foil is broker or missing.

DIST. BY: PROCTER & GAMBLE,

CINCINNATI, OH 45202

PRINCIPAL DISPLAY PANEL

MULTI-SYMPTOM
Rolaids®
ADVANCED
ANTACID + ANTI-GAS

GOES TO WORK INSTANTLY

HEARTBURN + GAS
60 Chewable Tablets
Wild Berry